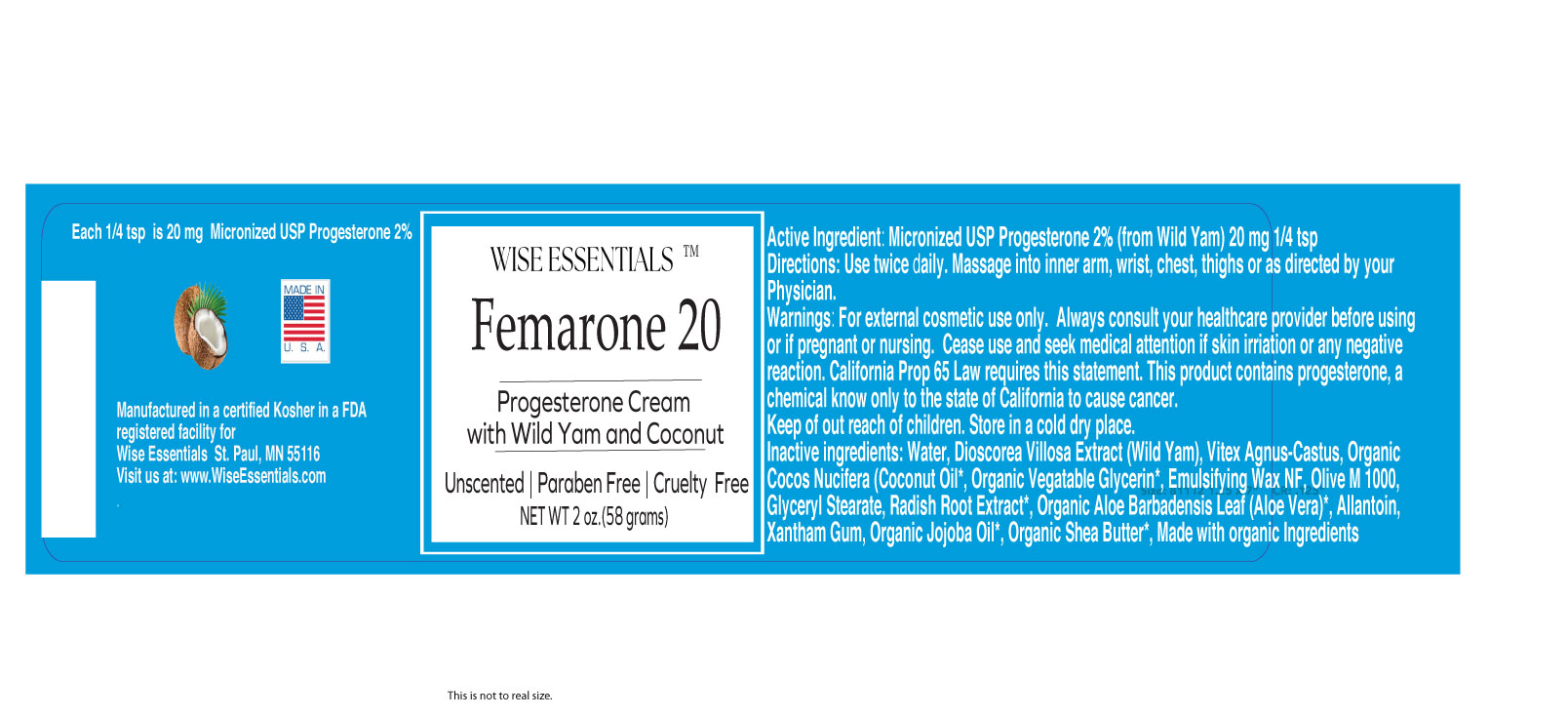 DRUG LABEL: Femarone 20
NDC: 87250-001 | Form: CREAM
Manufacturer: Wise Essentials LLC
Category: otc | Type: HUMAN OTC DRUG LABEL
Date: 20251213

ACTIVE INGREDIENTS: PROGESTERONE 20 mg/58 g
INACTIVE INGREDIENTS: CHASTE TREE FRUIT 2.5 mg/58 g; COCOS NUCIFERA (COCONUT) OIL 40 mg/58 g; JOJOBA OIL 5 mg/58 g; GLYCERIN 30 mg/58 g; SORBITAN OLIVATE 20 mg/58 g; DIOSCOREA VILLOSA TUBER 80 mg/58 g; ALLANTOIN 2.5 mg/58 g; RADISH 2.5 mg/58 g

Fermarone 20

RECENT MAJOR CHANGES

Femarone 20

DRUG FACTS Active Ingredient

Micronized Progesterone USP (Wild Yam 2%)

Uses This topical cream contains USP progesterone derived from wild yam. Applied to the skin may help balance your hormones and provide support for peri-menopause and menopause symptoms.

20 mg per p1/4 tsp of USP progesterone.

Inactive Ingredients:
Water, Dioscorea Villosa Extract (Wild Yam), Vitex Agnus-Castus, Organic Cocos Nucifera (Coconut Oil*, Organic Vegetable Glycerin*, Emulsifying Wax NF, Olive M 1000, Glyceryl Stearate, Radish Root Extract*, Organic Aloe Barbadensis Leaf (Aloe Vera)*, Allantoin, Xanthan Gum, Organic Jojoba Oil*, Organic Shea Butter*, Made with organic Ingredients
Warnings: For external cosmetic use only. Always consult your healthcare provider before using. Cease use and seek medical attention if skin irritation you or any negative reaction. If pregnant or nursing, consult a healthcare professional before use.

California Prop 65 Law requires this statement. This product contains progesterone, a chemical known only to the State of California to cause cancer.

Keep out of reach of children

Store in a cold, dry place

Directions: Use twice daily. Massage into inner arms, wrist, chest, or thighs or as directed by your Physician.

Questions? support@wiseessentials.com

Wise Essentials, St. Paul, MN 55116

www.WiseEssentials.com

MADE IN

Distributed and Manufactured in a certified

Kosher and FDA registered facility for

Wise Essentials St. Paul, MN 55116

Visit us at: www.WiseEssentials.com

Active Ingredient

Micronized Progesterone USP, (Wild Yam) 2%

DISCLAIMER

Disclaimer: This drug has not been found by FDA to be safe and effective, and this labeling has not been approved by FDA. For further information about unapproved drugs For further information about unapproved drugs, https://www.fda.gov/drugs/enforcement-activities-fda/unapproved-drugs

PURPOSE

This is a topical cream that contains bio-identical micronized USP progesterone derived from wild yam, blended with phytoestrogens. When applied topically to the skin, it may help to balance your hormones, and also to provide support for peri menopause and menopausal symptoms.

INDICATIONS AND USAGE

USES: This is a topical cream that contains bio-identical micronized USP progesterone derived from wild yam, blended with phytoestrogens. When applied topically to the skin, it may help to balance your hormones and also to provide support for perimenopause and menopause.

Apply once or twice a day. Massage into wrists, inner arms, thighs, chest, or apply or use as directed by your physician.

PREGNANCY OR BREASTFEEDING

If pregnant or nursing or if you have a serious medical condition, consult a healthcare professional before using this product.

KEEP OUT OF REACH OF CHILDREN

DOSAGE & ADMINISTRATION

Apply once or twice a day. Massage into wrists, inner arms, thighs, chest, or apply to together or use as directed by your physician.

INACTIVE INGREDIENT

Water, Wild Yam Extract, Chaste Tree Berry, Coconut Oil Organic, Vegetable Glycerin USP, Emulsifying Wax NF, Olivem 1000, Glyceryl Stearate, Radish Root Extract, Aloe Vera Powder Organic, Jojoba Oil Organic, Allantoin, Shea Butter Organic

QUESTIONS?

Contact support@wiseessentials.com

SAFETY

Report Adverse Events click here https://www.accessdata.fda.gov/scripts/medwatch/

FDA Safety Recalls Click here https://www.fda.gov/safety/recalls-market-withdrawals-safety-alerts

Presence in Breast Milk Click here https://www.ncbi.nlm.nih.gov/books/NBK501345/

RELATED RESOURCES

Medline Plus. Click here https://vsearch.nlm.nih.gov/vivisimo/cgi-bin/query-meta?v:project=medlineplus&query=PROGESTERONE&_gl=1*f9papn*_ga*MTc2NTIwMjU3MS4xNzY1Njc2NTE5*_ga_7147EPK006*czE3NjU2NzY1MTgkbzEkZzEkdDE3NjU2NzY4NzEkajI1JGwwJGgw*_ga_P1FPTH9PL4*czE3NjU2NzY1MTgkbzEkZzEkdDE3NjU2NzY4NzEkajI1JGwwJGgw

Clinical Trials.Click here https://www.clinicaltrials.gov/search?term=PROGESTERONE&viewType=Table#classicRedirect

Biochemcical Date Summary. Click here. https://go.drugbank.com/drugs/DB00396

WARNINGS

WARNINGS: If pregnant or nursing or if you have a serious medical condition, consult a healthcare professional before using this product.
KEEP OUT OF REACH OF CHILDREN Store in a cool, dry place
Always consult your healthcare provider before using or if pregnant or nursing. Cease use and seek medical attention if skin irritation or a negative reaction.
Keep out of reach of children. Store in a cool, dry place.
California Prop 65 Law requires this statement: This product contains progesterone,
a chemical known only to the State of California to cause cancer. Cease using this product
and seek medical attention if skin irritation or other negative reactions occur.